DRUG LABEL: Vitamin A and D
NDC: 69396-121 | Form: OINTMENT
Manufacturer: Trifecta Pharmaceuticals USA LLC
Category: otc | Type: HUMAN OTC DRUG LABEL
Date: 20241231

ACTIVE INGREDIENTS: PETROLATUM 76 g/100 g
INACTIVE INGREDIENTS: MINERAL OIL; VITAMIN A PALMITATE; CHOLECALCIFEROL; MICROCRYSTALLINE WAX; PARAFFIN

Globe Vitamin A & D Ointment

Active Ingredient

Petrolatum 76%

Purpose

Skin Protectant

Uses

Temporarily protects and relieves

- minor cuts
- scrapes
- burns
- chapped or cracked skin and lips

Stop use and ask a doctor

Condition worsens

Symptoms last more than 7 days or clear up and occur again with a few days

Keep out of reach of children

If swallowed, get medical help or contact a Poison Control Center immediately

When using this product

Avoid contact with eyes

Do Not Use

- On deep or puncture wounds
- Animal Bites
- Serious Burns

Directions

Apply as needed

Inactive ingredients

mineral oil, vitamin A Palmitate, vitamin D3, Microcrystalline Wax, Paraffin

Distributed By

Trifecta Pharmaceuticals USA

101 NE Third Avenue, Suite 1500

Ft. Lauderdale, FL. 33301

www.trifecta-pharma.com

1-888-296-9067

Warnings

For external use only

Questions

Call: 1-888-296-9067

STORAGE AND HANDLING

Store at room temperature 20º-25ºC (68º-77ºF)

Tamper evident, do not use if packet is torn, cut or opened

Avoid excessive heat and humidity